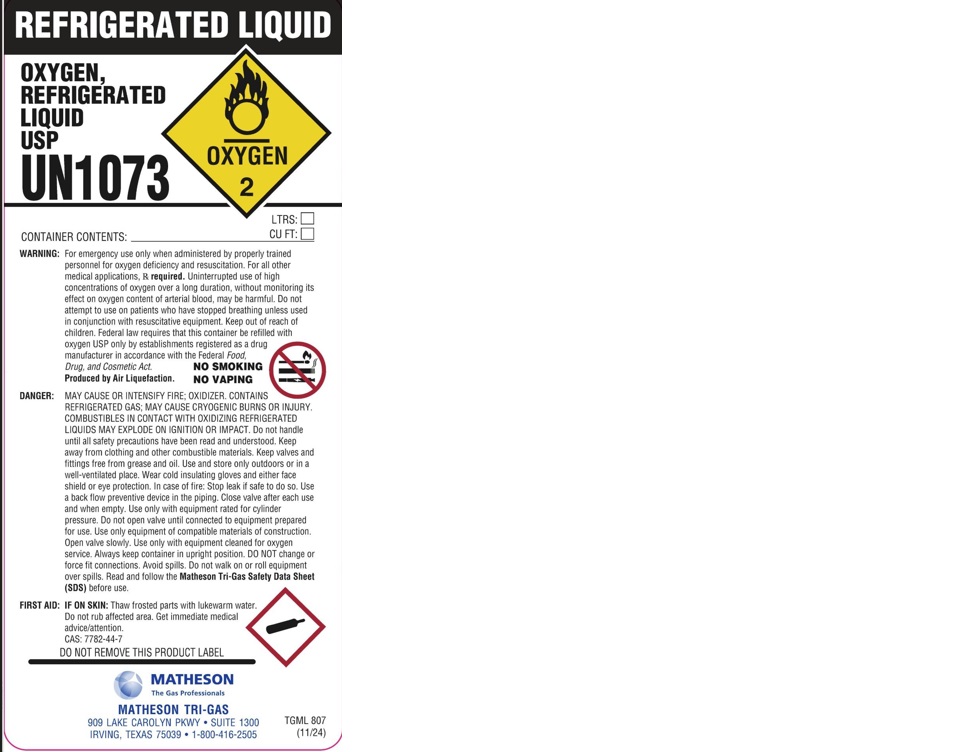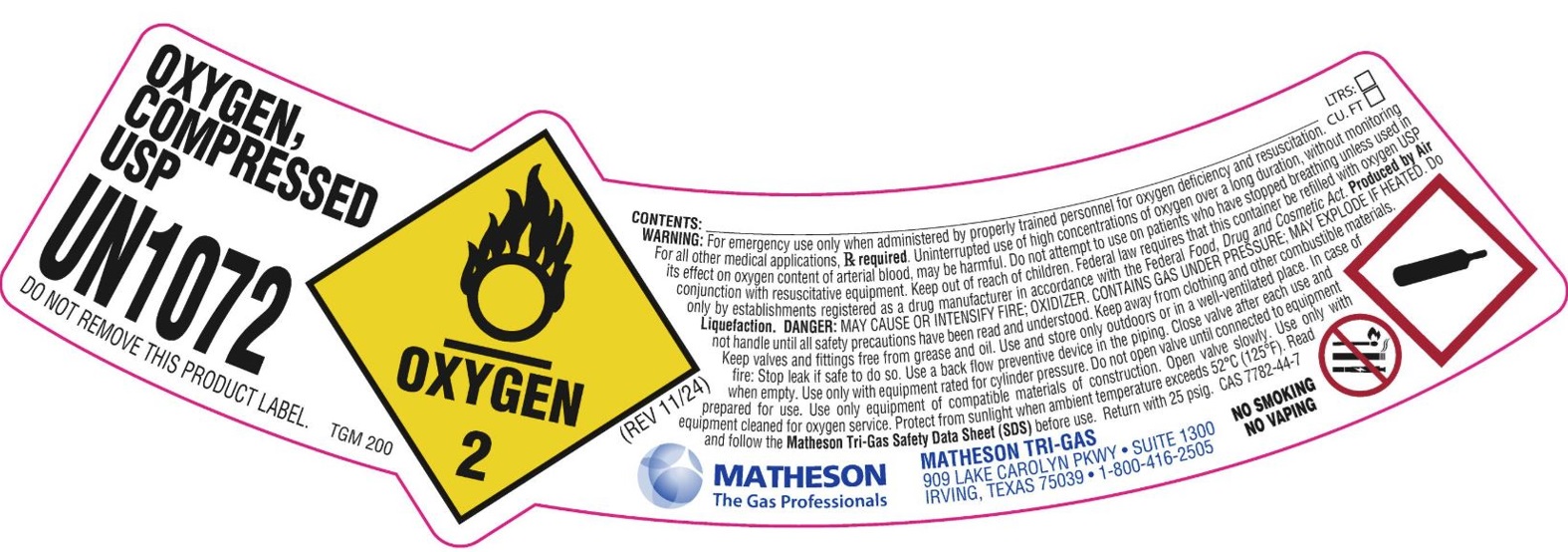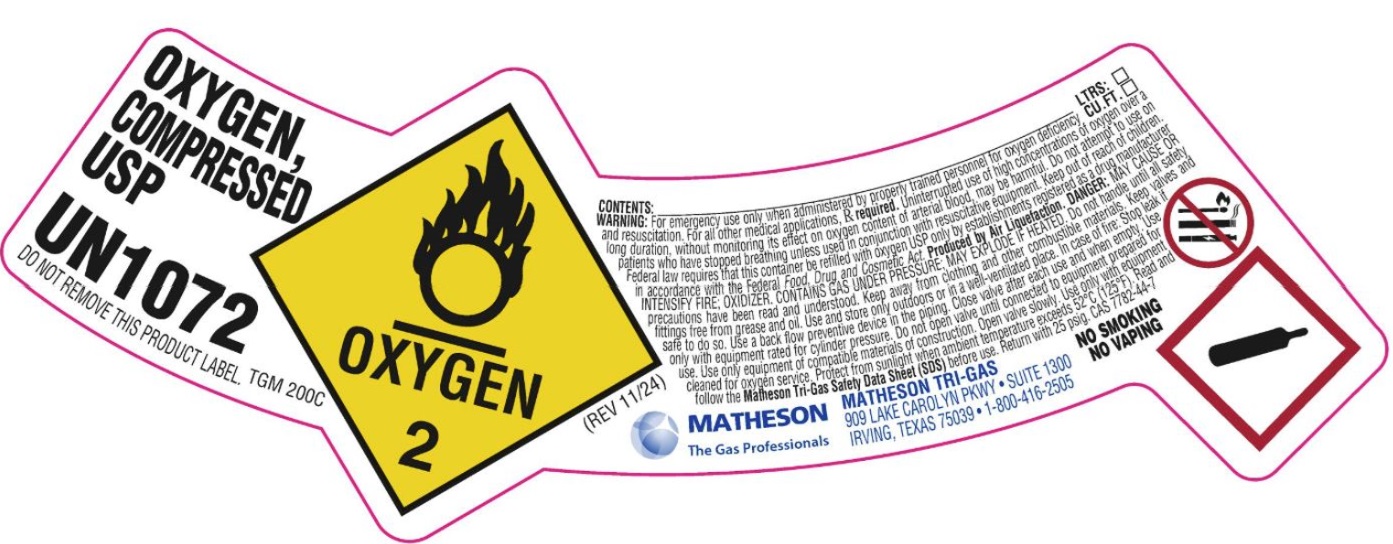 DRUG LABEL: Oxygen
NDC: 55037-113 | Form: GAS
Manufacturer: Matheson Tri-Gas, Inc.
Category: prescription | Type: HUMAN PRESCRIPTION DRUG LABEL
Date: 20260121

ACTIVE INGREDIENTS: OXYGEN 992 mL/1 L

Oxygen

PACKAGE LABEL

OXYGEN, COMPRESSED USP

UN1072

DO NOT REMOVE THIS PRODUCT LABEL.

CONTENTS:

LTERS:

CU. FT

WARNING: For emergency use only when administered by properly trained personnel for oxygen deficiency and resuscitation. For all other medical applications, Rx required. Uninterrupted use of high concentrations of oxygen over a long duration, without monitoring its effect on oxygen content of arterial blood, may be harmful. Do not attempt to use on patients who have stopped breathing unless used in conjunction with resuscitative equipment. Keep out of reach of children. Federal law requires that this container be refilled with oxygen USP only by establishments registered as a drug manufacturer in accordance with the Federal Food, Drug and Cosmetic Act. Produced by Air Liquefaction. DANGER: MAY CAUSE OR INTENSIFY FIRE; OXIDIZER. CONTAINS GAS UNDER PRESSURE; MAY EXPLODE IF HEATED. Do not handle until all safety precautions have been read and understood. Keep away from clothing and other combustible materials. Keep valves and fittings free from grease and oil. Use and store only outdoors or in a well-ventilated place. In case of fire: Stop leak if safe to do so. Use a back flow preventive device in the piping. Close valve after each use and when empty. Use only with equipment rated for cylinder pressure. Do not open valve until connected to equipment prepared for use. Use only equipment of compatible materials of construction. Open valve slowly. Use only with equipment cleaned for oxygen service. Protect from sunlight when ambient temperature exceeds 52 C (125 F). Read and follow the Matheson Tri-Gas Safety Data Sheet (SDS) before use. Return with 25 psig. CAS 7782-44-7

MATHESON

The Gas Professionals

MATHESON TRI-GAS

909 LAKE CAROLYN PKWY. SUITE 1300

IRVING, TEXAS 75039 1-800-416-2505

NO SMOKING

NO VAPING

PACKAGE LABEL

REFRIGERATED LIQUID

OXYGEN, REFRIGERATED LIQUID USP

UN1073

CONTAINER CONTENTS:

LTRS:

CU FT:

WARNING: For emergency use only when administered by properly trained personnel for oxygen deficiency and resuscitation. For all other medical applications, Rx required. Uninterrupted use of high concentrations of oxygen over a long duration, without monitoring its effect on oxygen content of arterial blood, may be harmful. Do not attempt to use on patients who have stopped breathing unless used in conjunction with resuscitative equipment. Keep out of reach of children. Federal law requires that this container be refilled with oxygen USP only by establishments registered as a drug manufacturer in accordance with the Federal Food, Drug, and Cosmetic Act. Produced by Air Liquefaction.

NO SMOKING

NO VAPING

DANGER: MAY CAUSE OR INTENSIFY FIRE; OXIDIZER. CONTAINS REFRIGERATED GAS; MAY CAUSE CRYOGENIC BURNS OR INJURY. COMBUSTIBLES IN CONTACT WITH OXIDIZING REFRIGERATED LIQUIDS MAY EXPLODE ON IGNITION OR IMPACT. Do not handle until all safety precautions have been read and understood. Keep away from clothing and other combustible materials. Keep valves and fittings free from grease and oil. Use and store only outdoors or in a well-ventilated place. Wear cold insulating gloves and either face shield or eye protection. In case of fire: Stop leak if safe to do so. Use a back flow preventive device in the piping. Close valve after each use and when empty. Use only with equipment rated for cylinder pressure. Do not open valve until connected to equipment prepared for use. Use only equipment of compatible materials of construction. Open valve slowly. Use only with equipment cleaned for oxygen service. Always keep container in upright position. DO NOT change or force fit connections. Avoid spills. Do not walk on or roll equipment over spills. Read and follow the Matheson Tri-Gas Safety Data Sheet (SDS) before use.

FIRST AID: IF ON SKIN: Thaw frosted parts with lukewarm water. Do not rub affected area. Get immediate medical advice/attention.

CAS: 7782-44-7

DO NOT REMOVE THIS PRODUCT LABEL

MATHESON

The Gas Professionals

MATHESON TRI-GAS

909 LAKE CAROLYN PKWY. SUITE 1300

IRVING, TEXAS 75039 1-800-416-2505

NO SMOKING

NO VAPING